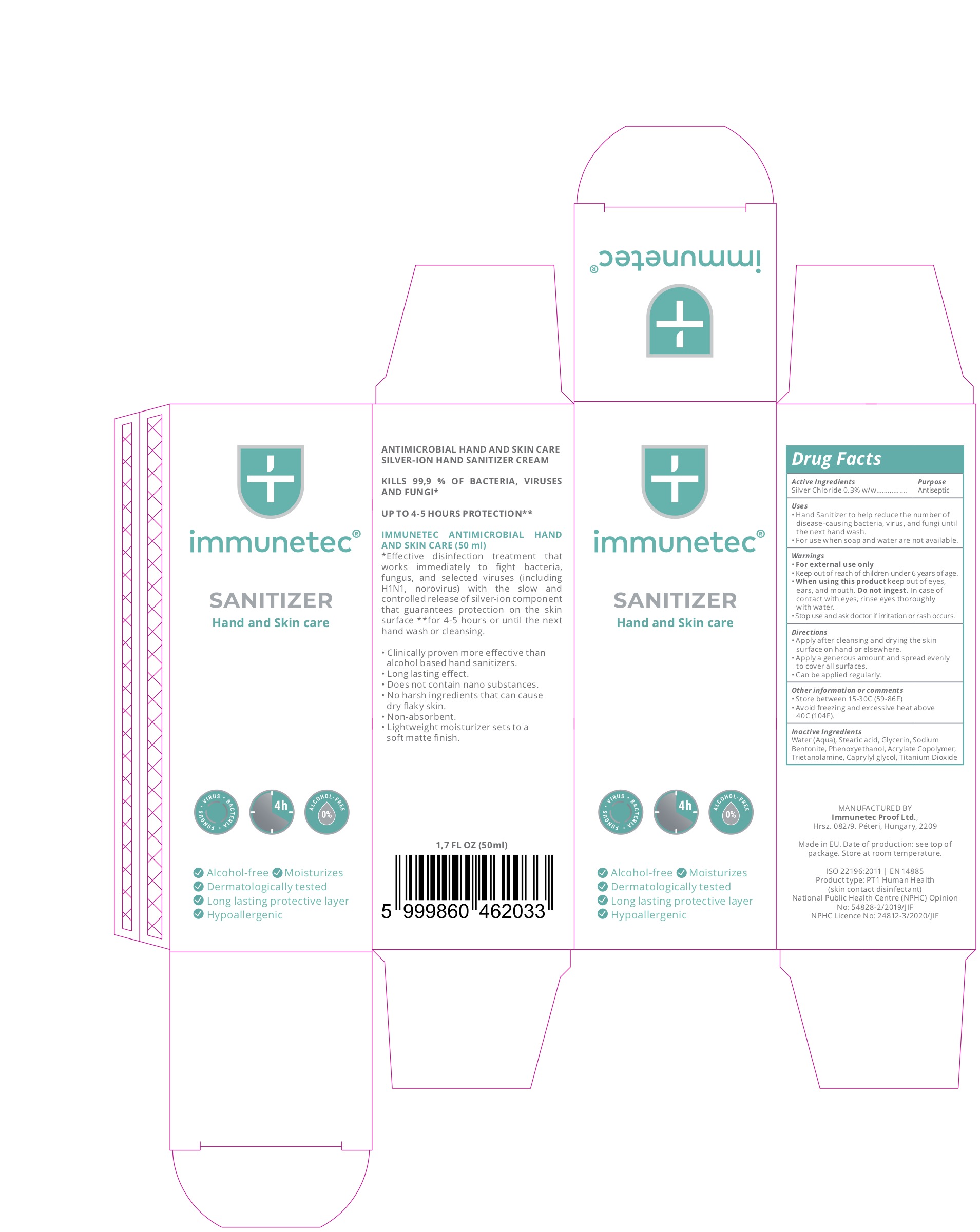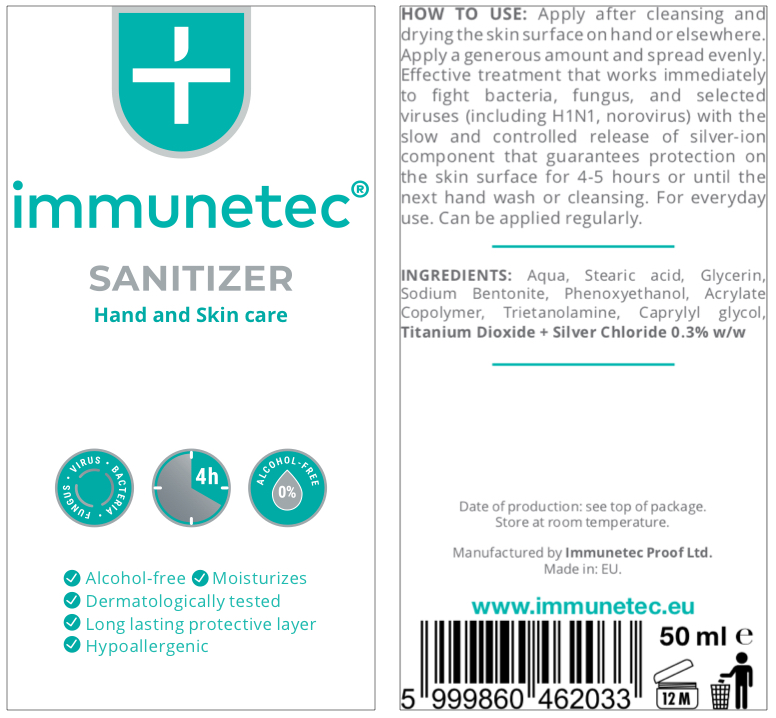 DRUG LABEL: Sanitizer Hand and Skin Care
NDC: 81541-001 | Form: CREAM
Manufacturer: Immunetec Proof Ltd.
Category: otc | Type: HUMAN OTC DRUG LABEL
Date: 20210212

ACTIVE INGREDIENTS: SILVER CHLORIDE 0.3 g/100 g
INACTIVE INGREDIENTS: WATER; ACRYLIC ACID/DIMETHICONE METHACRYLATE/ETHYLHEXYL ACRYLATE COPOLYMER; TROLAMINE; CAPRYLYL GLYCOL; GLYCERIN; SODIUM BENTONITE; STEARIC ACID; PHENOXYETHANOL; TITANIUM DIOXIDE

Immunetec Hand Sanitizer

Active Ingredient

Silver Chloride 0.3% w/w

Purpose

Antiseptic

Uses

To help reduce the number of disease-causing bacteria, virus, and fungi until the next hand wash.

For use when soap and water are not available.

Warnings

For external use only.

Keep out of reach of children under 6 years of age.

When using this product:

- keep out of eyes, ears, and mouth.
- Do not ingest.
- In case of contact with eyes, rinse eyes thoroughly with water.

Stop use and ask a doctor if irritation or rash occurs.

Directions

• Apply after cleansing and drying the skin surface on hand or elsewhere.

• Apply a generous amount and spread evenly to cover all surfaces.

• Can be applied regularly.

Other information or comments

• Store between 15-30 C (59-86 F)
• Avoid freezing and excessive heat above 40 C (104 F).

Inactive Ingredients

Water (Aqua), Stearic acid, Glycerin, Sodium bentonite, Phenoxyethanol, Acrylate copolymer, Triethanolamine, Caprylyl glycol, Titanium dioxide

Principal Display Panel

Sanitizer Hand and Skin Care (50 mL), NDC: 81541-001-01

Outer Package (Box)

Inner Package (Tube)